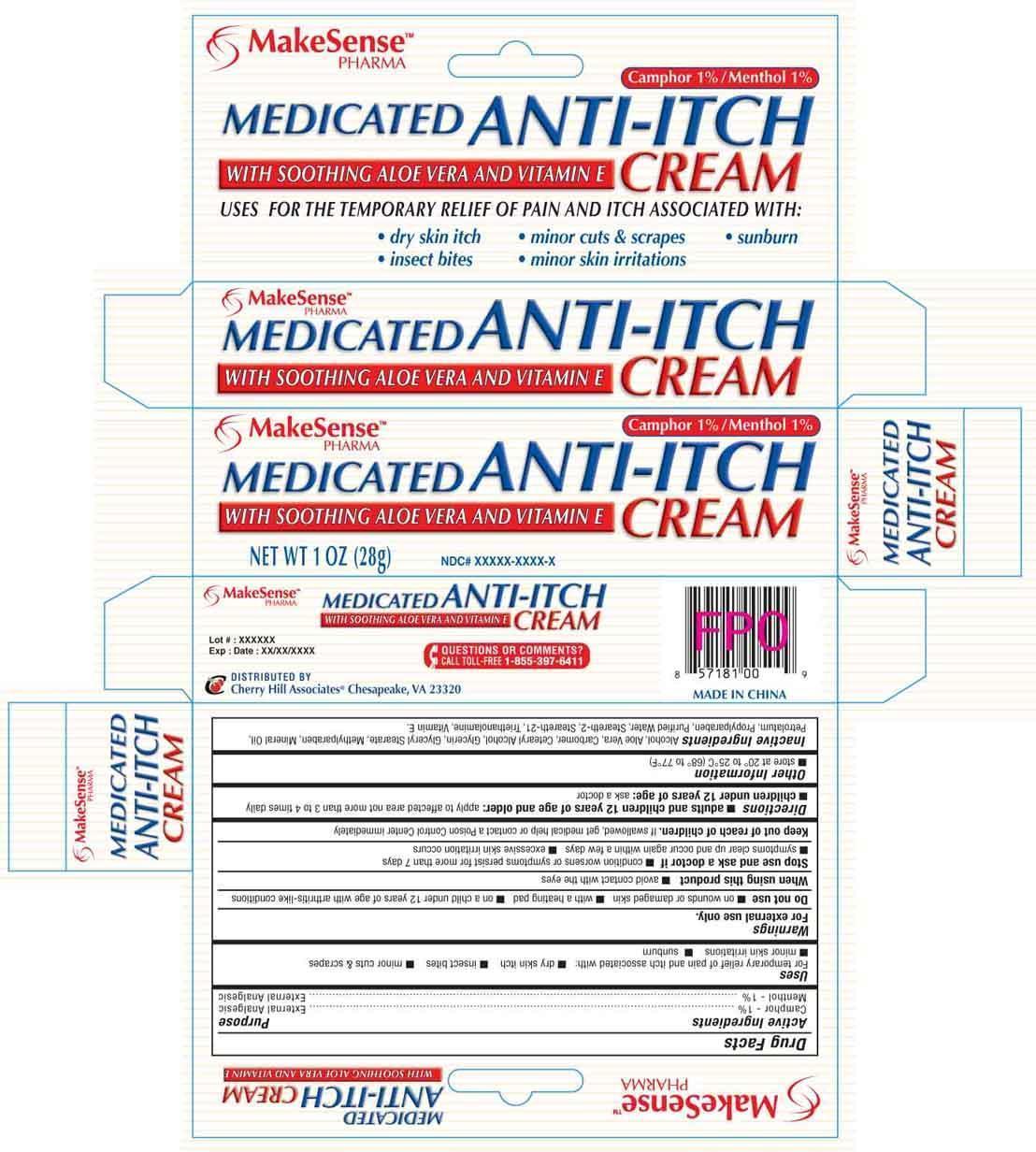 DRUG LABEL: MAKESENSE
NDC: 69020-201 | Form: CREAM
Manufacturer: Cherry Hill Sales Co
Category: otc | Type: HUMAN OTC DRUG LABEL
Date: 20140626

ACTIVE INGREDIENTS: CAMPHOR (SYNTHETIC) 1 g/100 g; MENTHOL 1 g/100 g
INACTIVE INGREDIENTS: ALCOHOL; ALOE VERA LEAF; CETOSTEARYL ALCOHOL; GLYCERIN; GLYCERYL STEARATE SE; METHYLPARABEN; MINERAL OIL; PETROLATUM; PROPYLPARABEN; WATER; STEARETH-2; STEARETH-21; TROLAMINE; ALPHA-TOCOPHEROL

Drug Facts

Active Ingredients

Camphor 1%

Menthol 1%

Purpose

External analgesic

External Analgesic

Uses

For temporary relief of pain and itch associated with ■ dry skin itch ■ insect bites ■ minor cuts & scrapes ■ minor skin irritations
■ sunburn

Warnings

For external use only

Do not use

■

■ on wounds or damaged skin ■ with a heating pad ■ on a child under 12 years of age with arthritis-like conditions

When using this product

■ avoid contact with the eyes

Stop use and ask a doctor

■ condition worsens or if symptoms persist for more than 7 days ■ symptoms clear up and occur again within a few days ■ excessive skin irritation occurs

Keep out of reach of children

If swallowed, get medical help or contact a Poison Control Center right away

Directions

■ adults and children 12 years of age and older: apply to affected area not more than 3 to 4 times daily
■ children under 12 years of age: ask a doctor

Other Information

■ store at 20 to 25C (68 to 77F)

Inactive Ingredients

Alcohol, Aloe Vera, Carbomer, Cetearyl Alcohol, Glycerin, Glyceryl Stearate, Methylparaben, Mineral Oil, Petrolatum, Propylparaben, Purified Water, Steareth-2, Steareth-21, Triethanolamine, Vitamin E.